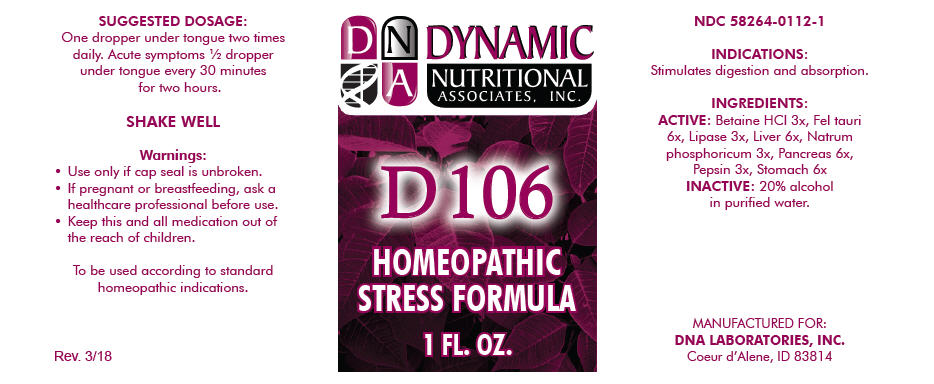 DRUG LABEL: D-106
NDC: 58264-0112 | Form: SOLUTION
Manufacturer: DNA Labs, Inc.
Category: homeopathic | Type: HUMAN OTC DRUG LABEL
Date: 20250113

ACTIVE INGREDIENTS: BETAINE HYDROCHLORIDE 3 [hp_X]/1 mL; BOS TAURUS BILE 6 [hp_X]/1 mL; PANCRELIPASE LIPASE 3 [hp_X]/1 mL; BEEF LIVER 6 [hp_X]/1 mL; SODIUM PHOSPHATE, DIBASIC, HEPTAHYDRATE 3 [hp_X]/1 mL; BOS TAURUS PANCREAS 6 [hp_X]/1 mL; PEPSIN 3 [hp_X]/1 mL; SUS SCROFA STOMACH 6 [hp_X]/1 mL
INACTIVE INGREDIENTS: ALCOHOL; WATER

D-106

NDC 58264-0112-1

INDICATIONS

PURPOSE

Stimulates digestion and absorption.

INGREDIENTS

ACTIVE

Betaine HCl 3x, Fel tauri 6x, Lipase 3x, Liver 6x, Natrum phosphoricum 3x, Pancreas 6x, Pepsin 3x, Stomach 6x

INACTIVE

20% alcohol in purified water.

SUGGESTED DOSAGE

One dropper under tongue two times daily. Acute symptoms ½ dropper under tongue every 30 minutes for two hours.

STORAGE AND HANDLING

SHAKE WELL

Warnings

- Use only if cap seal is unbroken.

PREGNANCY OR BREAST FEEDING

- If pregnant or breastfeeding, ask a healthcare professional before use.

KEEP OUT OF REACH OF CHILDREN

- Keep this and all medication out of the reach of children.

To be used according to standard homeopathic indications.

PRINCIPAL DISPLAY PANEL - 1 FL. OZ. Bottle Label

DYNAMIC
NUTRITIONAL
ASSOCIATES, INC.

D 106

HOMEOPATHIC
STRESS FORMULA

1 FL. OZ.